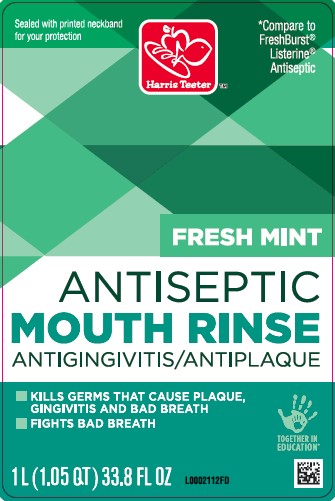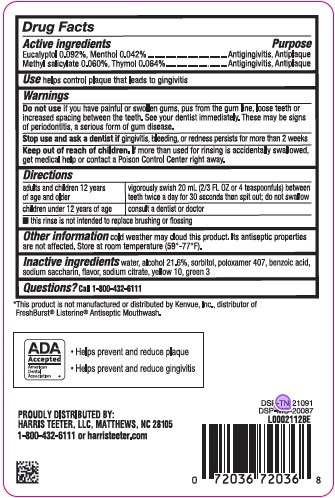 DRUG LABEL: Antiseptic Mouth Rinse
NDC: 72036-072 | Form: MOUTHWASH
Manufacturer: HARRIS TEETER
Category: otc | Type: HUMAN OTC DRUG LABEL
Date: 20260204

ACTIVE INGREDIENTS: EUCALYPTOL 0.92 mg/1 mL; MENTHOL 0.42 mg/1 mL; METHYL SALICYLATE 0.6 mg/1 mL; THYMOL 0.64 mg/1 mL
INACTIVE INGREDIENTS: WATER; ALCOHOL; SORBITOL; POLOXAMER 407; BENZOIC ACID; SACCHARIN SODIUM; SODIUM CITRATE; D&C YELLOW NO. 10; FD&C GREEN NO. 3

Harris Teeter 072.003/072AL-AN
Spring Mint Antiseptic Mouthrinse

Active Ingredients

Eucalyptol 0.092%

Menthol 0.042%

Methyl salicylate 0.060%

Thymol 0.064%

Purpose

Antigingivitis, Antiplaque

Use

helps control plaque that leads to gingivitis

Warnings

for this product

Do not use

if you have painful or swollen gums, pus from the gum line, loose teeth or increased spacing between the teeth. See your dentist immediately. These may be signs of periodontitis, a serious form of gum disease.

Stop use and ask a dentist if

gingivitis, bleeding, or redness persists for more than 2 weeks.

Keep out of reach of children.

If more than used for rinsing is accidentally swallowed, get medical help or contact a Poison Control Center right away.

Directions

Adults and children 12 years of age and older - Vigorously swish 20 ml (2/3 FL OZ or 4 teaspoonfuls) between teeth twice a day for 30 seconds then spit out; do not swallow
Children under 12 years of age - Consult a dentist or doctor

- This rinse is not intended to replace brushing or flossing

Other information

cold weather may cloud this product. Its antiseptic properties are not affected. Store at room temperature (59⁰ - 77⁰F).

Inactive ingredients

water, alcohol 21.6%, sorbitol, poloxamer 407, benzoic acid, sodium saccharin, flavor, sodium citrate, yellow 10, green 3

Questions?

Call 1-800-432-6111

Disclaimer

*This product is not manufactured or distributed by Kenvue, Inc., distributor of FreshBurst®Listerine®Antiseptic Mouthwash.

ADVERSE REACTION

ADA Accepted

American Dental Association

- Helps prevent and reduce plaque
- Helps prevent and reduce gingivitis

Proudly Distributed by:

Harris Teeter, LLC, Matthews, NC 28105

1-800-432-6111 or harristeeter.com

DSP-TN-21091
DSP-MO-20087

Principal Panel Display

Sealed With Printed Neckband For Your Protection

Harris Teeter™

*Compare to FreshBurst®Listerine® Antiseptic

FRESH MINT

ANTISEPTIC

MOUTH RINSE

ANTIGINGIVITIS/ANTIPLAQUE

- Kills germs that cause plaque, gingivitis and bad breath
- Fights bad breath

1 L (1.05 QT) 33.8 FL OZ

TOGETHER IN EDUCATION®